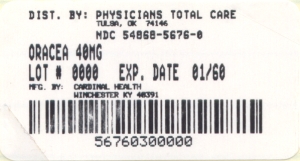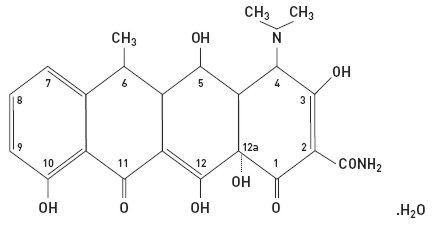 DRUG LABEL: Oracea
NDC: 54868-5676 | Form: CAPSULE, DELAYED RELEASE PELLETS
Manufacturer: Physicians Total Care, Inc.
Category: prescription | Type: HUMAN PRESCRIPTION DRUG LABEL
Date: 20091230

ACTIVE INGREDIENTS: DOXYCYCLINE 40 mg/1 1
INACTIVE INGREDIENTS: HYPROMELLOSE; FERRIC OXIDE RED; FERRIC OXIDE YELLOW; METHACRYLIC ACID - ETHYL ACRYLATE COPOLYMER (1:1) TYPE A; POLYETHYLENE GLYCOL; POLYSORBATE 80; TALC; TITANIUM DIOXIDE; TRIETHYL CITRATE

40 mg*

*
30* mg Immediate Release & 10 mg Delayed Release beads

Rx Only

KEEP OUT OF REACH OF CHILDREN

The dosage of ORACEA differs from that of doxycycline used to treat infections. To reduce the development of resistant bacteria as well as to maintain the effectiveness of other antibacterial drugs, ORACEA should be used only as indicated.

ORACEA is indicated for the treatment of only inflammatory lesions (papules and pustules) of rosacea in adult patients.

This formulation of doxycycline has not been evaluated as an antibacterial in the treatment of infections.

DESCRIPTION

ORACEA (doxycycline, USP) capsules 40 mg are hard gelatin capsule shells filled with two types of doxycycline beads (30 mg immediate release and 10 mg delayed release) that together provide a dose of 40 mg of anhydrous doxycycline (C22H24N2O8).

The structural formula of doxycycline, USP is:

with an empirical formula of C22H24N2O8•H2O and a molecular weight of 462.46. The chemical designation for doxycycline is 2-Naphthacenecarboxamide, 4-(dimethylamino)-1,4,4a,5,5a,6,11,12a-octahydro-3,5,10,12,12a-pentahydroxy-6-methyl-1,11-dioxo-, [4S-(4aα, 4aα, 5α, 5aα, 6a,12aα)]-, monohydrate. It is very slightly soluble in water.

Inert ingredients in the formulation are: hypromellose, iron oxide red, iron oxide yellow, methacrylic acid copolymer, polyethylene glycol, Polysorbate 80, sugar spheres, talc, titanium dioxide, and triethyl citrate. Active ingredients: Each capsule contains doxycycline, USP in an amount equivalent to 40 mg of anhydrous doxycycline.

CLINICAL PHARMACOLOGY

ORACEA capsules are not bioequivalent to other doxycycline products. The pharmacokinetics of doxycycline following oral administration of ORACEA was investigated in 2 volunteer studies involving 61 adults. Pharmacokinetic parameters for ORACEA following single oral doses and at steady-state in healthy subjects are presented in Table 1.

Table 1. Pharmacokinetic Parameters [Mean (± SD)] for ORACEA
 | N | Cmax * (ng/mL) | Tmax ** (hr) | AUC0-∞ * (ng∙hr/mL) | t1/2 (hr) *
Single Dose 40 mg capsules | 30 | 510 ± 220.7 | 3.00 (1.0-4.1) | 9227 ± 3212.8 | 21.2 ± 7.6
Steady-State *** 40 mg capsules | 31 | 600 ± 194.2 | 2.00 (1.0-4.0) | 7543 ± 2443.9 | 23.2 ± 6.2

* Mean
** Median
*** Day 7
Absorption

In a single-dose food-effect study involving administration of ORACEA to healthy volunteers, concomitant administration with a 1000 calorie, high-fat, high-protein meal that included dairy products, resulted in a decrease in the rate and extent of absorption (Cmax and AUC) by about 45% and 22%, respectively, compared to dosing under fasted conditions. This decrease in systemic exposure can be clinically significant, and therefore if ORACEA is taken close to meal times, it is recommended that it be taken at least one hour prior to or two hours after meals.

Distribution

Doxycycline is greater than 90% bound to plasma proteins.

Metabolism

Major metabolites of doxycycline have not been identified. However, enzyme inducers such as barbiturates, carbamazepine, and phenytoin decrease the half-life of doxycycline.

Excretion

Doxycycline is excreted in the urine and feces as unchanged drug. It is reported that between 29% and 55.4% of an administered dose can be accounted for in the urine by 72 hours. Terminal half-life averaged 21.2 hours in subjects receiving a single dose of ORACEA.

Special Populations Geriatric

Doxycycline pharmacokinetics have not been evaluated in geriatric patients.

Pediatric

Doxycycline pharmacokinetics have not been evaluated in pediatric patients (see WARNINGS section).

Gender

The pharmacokinetics of ORACEA were compared in 16 male and 14 female subjects under fed and fasted conditions. While female subjects had a higher Cmax and AUC than male subjects, these differences were thought to be due to differences in body weight/lean body mass.

Race

Differences in doxycycline pharmacokinetics among racial groups have not been evaluated.

Renal Insufficiency

Studies have shown no significant difference in serum half-life of doxycycline in patients with normal and severely impaired renal function. Hemodialysis does not alter the serum half-life of doxycycline.

Hepatic Insufficiency

Doxycycline pharmacokinetics have not been evaluated in patients with hepatic insufficiency.

Gastric Insufficiency

In a study in healthy volunteers (N=24) the bioavailability of doxycycline is reported to be reduced at high pH. This reduced bioavailability may be clinically significant in patients with gastrectomy, gastric bypass surgery or who are otherwise deemed achlorhydric.

Drug Interactions

(see PRECAUTIONS section)

MICROBIOLOGY

Doxycycline is a member of the tetracycline class of antibacterial drugs. The plasma concentrations of doxycycline achieved with ORACEA during administration (see CLINICAL PHARMACOLOGY and DOSAGE AND ADMINISTRATION) are less than the concentration required to treat bacterial diseases. In vivo microbiological studies utilizing a similar drug exposure for up to 18 months demonstrated no detectable long-term effects on bacterial flora of the oral cavity, skin, intestinal tract, and vagina.

ORACEA should not be used for treating bacterial infections, providing antibacterial prophylaxis, or reducing the numbers or eliminating microorganisms associated with any bacterial disease.

CLINICAL STUDIES

The safety and efficacy of ORACEA in the treatment of only inflammatory lesions (papules and pustules) of rosacea was evaluated in two randomized, placebo-controlled, multi-centered, double-blind, 16-week Phase 3 studies involving 537 patients (total of 269 patients on ORACEA from the two studies) with rosacea (10 to 40 papules and pustules and two or fewer nodules). Pregnant and nursing women, patients less than 18 years of age, and patients with ocular rosacea and/or blepharitis/meibomianitis who require ophthalmologic treatment were excluded from study. Mean baseline lesion counts were 20 and 21 for ORACEA and placebo patient groups respectively.

At Week 16, patients in the ORACEA group were evaluated using co-primary endpoints of mean reduction in lesion counts and a dichotomized static Investigator's Global Assessment of Clear or Almost Clear (defined as 1 to 2 small papules or pustules) when compared to the placebo group in both Phase 3 studies.

Table 2: Clinical Results of ORACEA versus Placebo
 |  | Study 1 |  |  | Study 2
 | ORACEA 40 mg N = 127 |  | Placebo N = 124 | ORACEA 40 mg N = 142 |  | Placebo N = 144
Mean Change in Lesion Count from Baseline | -11.8 |  | -5.9 | -9.5 |  | -4.3
No (%) of Subjects Clear or Almost Clear in the IGA * | 39 (30.7%) |  | 24 (19.4%) | 21 (14.8%) |  | 9 (6.3%)

* Investigator's Global Assessment
Patients treated with ORACEA did not demonstrate significant improvement in erythema when compared to those treated with placebo.

INDICATIONS AND USAGE

ORACEA is indicated for the treatment of only inflammatory lesions (papules and pustules) of rosacea in adult patients. No meaningful effect was demonstrated for generalized erythema (redness) of rosacea. ORACEA has not been evaluated for the treatment of the erythematous, telangiectatic, or ocular components of rosacea. Efficacy of ORACEA beyond 16 weeks and safety beyond 9 months have not been established.

This formulation of doxycycline has not been evaluated in the treatment or prevention of infections. ORACEA should not be used for treating bacterial infections, providing antibacterial prophylaxis, or reducing the numbers or eliminating microorganisms associated with any bacterial disease.

To reduce the development of drug-resistant bacteria as well as to maintain the effectiveness of other antibacterial drugs, ORACEA should be used only as indicated.

CONTRAINDICATIONS

This drug is contraindicated in persons who have shown hypersensitivity to doxycycline or any of the other tetracyclines.

WARNINGS

Teratogenic effects1) Doxycycline, like other tetracycline-class antibiotics, can cause fetal harm when administered to a pregnant woman. If any tetracycline is used during pregnancy or if the patient becomes pregnant while taking these drugs, the patient should be informed of the potential hazard to the fetus and treatment stopped immediately.
ORACEA should not be used during pregnancy (see PRECAUTIONS: Pregnancy). 2) The use of drugs of the tetracycline class during tooth development (last half of pregnancy, infancy, and childhood up to the age of 8 years) may cause permanent discoloration of the teeth (yellow-gray-brown). This adverse reaction is more common during long-term use of the drug but has been observed following repeated short-term courses. Enamel hypoplasia has also been reported. Tetracycline drugs, therefore, should not be used during tooth development unless other drugs are not likely to be effective or are contraindicated.3) All tetracyclines form a stable calcium complex in any bone-forming tissue. A decrease in fibula growth rate has been observed in premature human infants given oral tetracycline in doses of 25 mg/kg every 6 hours. This reaction was shown to be reversible when the drug was discontinued.

Results of animal studies indicate that tetracyclines cross the placenta, are found in fetal tissues, and can cause retardation of skeletal development on the developing fetus. Evidence of embryotoxicity has been noted in animals treated early in pregnancy (see PRECAUTIONS: Pregnancy section).

Gastrointestinal effects

Pseudomembranous colitis has been reported with nearly all antibacterial agents and may range from mild to life-threatening.

Therefore, it is important to consider this diagnosis in patients who present with diarrhea subsequent to the administration of antibacterial agents.

Treatment with antibacterial agents alters the normal flora of the colon and may permit overgrowth of clostridia. Studies indicate that a toxin produced by Clostridium difficile is a primary cause of "antibiotic-associated colitis".

If a diagnosis of pseudomembranous colitis has been established, therapeutic measures should be initiated. Mild cases of pseudomembranous colitis usually respond to discontinuation of the drug alone. In moderate to severe cases, consideration should be given to management with fluids and electrolytes, protein supplementation, and treatment with an antibacterial drug clinically effective against Clostridium difficile colitis.

Metabolic effects

The anti-anabolic action of the tetracyclines may cause an increase in BUN. While this is not a problem in those with normal renal function, in patients with significantly impaired function, higher serum levels of tetracycline-class antibiotics may lead to azotemia, hyperphosphatemia, and acidosis. If renal impairment exists, even usual oral or parenteral doses may lead to excessive systemic accumulations of the drug and possible liver toxicity. Under such conditions, lower than usual total doses are indicated, and if therapy is prolonged, serum level determinations of the drug may be advisable.

Photosensitivity

Photosensitivity manifested by an exaggerated sunburn reaction has been observed in some individuals taking tetracyclines. Although this was not observed during the duration of the clinical studies with ORACEA, patients should minimize or avoid exposure to natural or artificial sunlight (tanning beds or UVA/B treatment) while using ORACEA. If patients need to be outdoors while using ORACEA, they should wear loose-fitting clothes that protect skin from sun exposure and discuss other sun protection measures with their physician.

PRECAUTIONS

General

Safety of ORACEA beyond 9 months has not been established.

As with other antibiotic preparations, use of ORACEA may result in overgrowth of non-susceptible microorganisms, including fungi. If superinfection occurs, ORACEA should be discontinued and appropriate therapy instituted. Although not observed in clinical trials with ORACEA, the use of tetracyclines may increase the incidence of vaginal candidiasis.

ORACEA should be used with caution in patients with a history of or predisposition to candidiasis overgrowth.

Bacterial resistance to tetracyclines may develop in patients using ORACEA. Because of the potential for drug-resistant bacteria to develop during the use of ORACEA, it should be used only as indicated.

Autoimmune Syndromes

Tetracyclines have been associated with the development of autoimmune syndromes. Symptoms may be manifested by fever, rash, arthralgia, and malaise. In symptomatic patients, liver function tests, ANA, CBC, and other appropriate tests should be performed to evaluate the patients. Use of all tetracycline-class drugs should be discontinued immediately.

Tissue Hyperpigmentation

Tetracycline class antibiotics are known to cause hyperpigmentation. Tetracycline therapy may induce hyperpigmentation in many organs, including nails, bone, skin, eyes, thyroid, visceral tissue, oral cavity (teeth, mucosa, alveolar bone), sclerae and heart valves. Skin and oral pigmentation has been reported to occur independently of time or amount of drug administration, whereas other pigmentation has been reported to occur upon prolonged administration. Skin pigmentation includes diffuse pigmentation as well as over sites of scars or injury.

Pseudotumor cerebri

Bulging fontanels in infants and benign intracranial hypertension in adults have been reported in individuals receiving tetracyclines. These conditions disappeared when the drug was discontinued.

Information for Patients

See Patient Package Insert that accompanies this Package Insert for additional information to give patients.

1. Photosensitivity manifested by an exaggerated sunburn reaction has been observed in some individuals taking tetracyclines, including doxycycline. Patients should minimize or avoid exposure to natural or artificial sunlight (tanning beds or UVA/B treatment) while using doxycycline. If patients need to be outdoors while using doxycycline, they should wear loose-fitting clothes that protect skin from sun exposure and discuss other sun protection measures with their physician. Treatment should be discontinued at the first evidence of sunburn.
2. Concurrent use of doxycycline may render oral contraceptives less effective (see Drug Interactions).
3. Autoimmune syndromes, including drug-induced lupus-like syndrome, autoimmune hepatitis, vasculitis and serum sickness have been observed with tetracycline-class antibiotics, including doxycycline. Symptoms may be manifested by arthralgia, fever, rash and malaise. Patients who experience such symptoms should be cautioned to stop the drug immediately and seek medical help.
4. Patients should be counseled about discoloration of skin, scars, teeth or gums that can arise from doxycycline therapy.
5. Take ORACEA exactly as directed. Increasing doses beyond 40 mg every morning may increase the likelihood that bacteria will develop resistance and will not be treatable by other antibacterial drugs in the future.
6. It is recommended that ORACEA not be used by pregnant or breast feeding women. (see Carcinogenesis, Mutagenesis, Impairment of Fertility, Pregnancy and Nursing Mothers sections).
7. It is recommended that ORACEA not be used by individuals of either gender who are attempting to conceive a child (see Carcinogenesis, Mutagenesis, Impairment of Fertility, and Pregnancy sections).

Laboratory Tests

Periodic laboratory evaluations of organ systems, including hematopoietic, renal and hepatic studies should be performed. Appropriate tests for autoimmune syndromes should be performed as indicated.

Drug Interactions

1. Because tetracyclines have been shown to depress plasma prothrombin activity, patients who are on anticoagulant therapy may require downward adjustment of their anticoagulant dosage.
2. Since bacteriostatic drugs may interfere with the bactericidal action of penicillin, it is advisable to avoid giving tetracycline-class drugs in conjunction with penicillin.
3. The concurrent use of tetracycline and methoxyflurane has been reported to result in fatal renal toxicity.
4. Absorption of tetracyclines is impaired by bismuth subsalicylate, proton pump inhibitors, antacids containing aluminum, calcium or magnesium and iron-containing preparations.
5. Doxycycline may interfere with the effectiveness of low dose oral contraceptives. To avoid contraceptive failure, females are advised to use a second form of contraceptive during treatment with doxycycline.
6. There have been reports of pseudotumor cerebri (benign intracranial hypertension) associated with the concomitant use of isotretinoin and tetracyclines. Since both oral retinoids, including isotretinoin and acitretin, and the tetracyclines, primarily minocycline, can cause increased intracranial pressure, the concurrent use of an oral retinoid and a tetracycline should be avoided.

Drug/Laboratory Test Interactions

False elevations of urinary catecholamine levels may occur due to interference with the fluorescence test.

Carcinogenesis, Mutagenesis, Impairment of Fertility

Doxycycline was assessed for potential to induce carcinogenesis in a study in which the compound was administered to Sprague-Dawley rats by gavage at dosages of 20, 75, and 200 mg/kg/day for two years. An increased incidence of uterine polyps was observed in female rats that received 200 mg/kg/day, a dosage that resulted in a systemic exposure to doxycycline approximately 12.2 times that observed in female humans who use ORACEA (exposure comparison based upon area under the curve (AUC) values). No impact upon tumor incidence was observed in male rats at 200 mg/kg/day, or in either gender at the other dosages studied. Evidence of oncogenic activity was obtained in studies with related compounds, i.e., oxytetracycline (adrenal and pituitary tumors) and minocycline (thyroid tumors).

Doxycycline demonstrated no potential to cause genetic toxicity in an in vitro point mutation study with mammalian cells (CHO/HGPRT forward mutation assay) or in an in vivo micronucleus assay conducted in CD-1 mice. However, data from an in vitro assay with CHO cells for potential to cause chromosomal aberrations suggest that doxycycline is a weak clastogen.

Oral administration of doxycycline to male and female Sprague-Dawley rats adversely affected fertility and reproductive performance, as evidenced by increased time for mating to occur, reduced sperm motility, velocity, and concentration, abnormal sperm morphology, and increased pre- and post-implantation losses. Doxycycline induced reproductive toxicity at all dosages that were examined in this study, as even the lowest dosage tested (50 mg/kg/day) induced a statistically significant reduction in sperm velocity. Note that 50 mg/kg/day is approximately 3.6 times the amount of doxycycline contained in the recommended daily dose of ORACEA for a 60-kg human when compared on the basis of AUC estimates. Although doxycycline impairs the fertility of rats when administered at sufficient dosage, the effect of ORACEA on human fertility is unknown.

Pregnancy Teratogenic Effects Pregnancy Category D

(see WARNINGS section). Results from animal studies indicate that doxycycline crosses the placenta and is found in fetal tissues.

Nonteratogenic effects

(see WARNINGS section).

Labor and Delivery

The effect of tetracyclines on labor and delivery is unknown.

Nursing Mothers

Tetracyclines are excreted in human milk. Because of the potential for serious adverse reactions in infants from doxycycline, ORACEA should not be used in mothers who breastfeed. (see WARNINGS section).

Pediatric Use

ORACEA should not be used in infants and children less than 8 years of age (see WARNINGS section). ORACEA has not been studied in children of any age with regard to safety or efficacy, therefore use in children is not recommended.

ADVERSE REACTIONS

Adverse Reactions in Clinical Trials of ORACEA

In controlled clinical trials of adult patients with mild to moderate rosacea, 537 patients received ORACEA or placebo over a 16-week period. The most frequent adverse reactions occurring in these studies are listed in Table 3.

Table 3. Incidence (%) of Selected Adverse Reactions in Clinical Trials of ORACEA (n=269) vs. Placebo (n=268)
 | ORACEA | Placebo
Nasopharyngitis | 13 (4.8) | 9 (3.4)
Pharyngolaryngeal Pain | 3 (1.1) | 2 (0.7)
Sinusitis | 7 (2.6) | 2 (0.7)
Nasal Congestion | 4 (1.5) | 2 (0.7)
Fungal Infection | 5 (1.9) | 1 (0.4)
Influenza | 5 (1.9) | 3 (1.1)
Diarrhea | 12 (4.5) | 7 (2.6)
Abdominal Pain Upper | 5 (1.9) | 1 (0.4)
Abdominal Distention | 3 (1.1) | 1 (0.4)
Abdmonial Pain | 3 (1.1) | 1 (0.4)
Stomach Discomfort | 3 (1.1) | 2 (0.7)
Dry Mouth | 3 (1.1) | 0 (0)
Hypertension | 8 (3.0) | 2 (0.7)
Blood Pressure Increase | 4 (1.5) | 1 (0.4)
Aspartate Aminotransferase Increase | 6 (2.2) | 2 (0.7)
Blood Lactate Dehydrogenase Increase | 4 (1.5) | 1 (0.4)
Blood Glucose Increase | 3 (1.1) | 0 (0)
Anxiety | 4 (1.5) | 0 (0)
Pain | 4 (1.5) | 1 (0.4)
Back Pain | 3 (1.1) | 0 (0)
Sinus Headache | 3 (1.1) | 0 (0)

Note: Percentages based on total number of study participants in each treatment group.
Adverse Reactions for Tetracyclines

The following adverse reactions have been observed in patients receiving tetracyclines at higher, antimicrobial doses:

Gastrointestinal: anorexia, nausea, vomiting, diarrhea, glossitis, dysphagia, enterocolitis, and inflammatory lesions (with vaginal candidiasis) in the anogenital region. Hepatotoxicity has been reported rarely. Rare instances of esophagitis and esophageal ulcerations have been reported in patients receiving the capsule forms of the drugs in the tetracycline class. Most of the patients experiencing esophagitis and/or esophageal ulceration took their medication immediately before lying down. (see DOSAGE AND ADMINISTRATION section).

Skin: maculopapular and erythematous rashes. Exfoliative dermatitis has been reported but is uncommon. Photosensitivity is discussed above. (see WARNINGS section).

Renal toxicity: Rise in BUN has been reported and is apparently dose-related. (see WARNINGS section).

Hypersensitivity reactions: urticaria, angioneurotic edema, anaphylaxis, anaphylactoid purpura, serum sickness, pericarditis, and exacerbation of systemic lupus erythematosus.

Blood: Hemolytic anemia, thrombocytopenia, neutropenia, and eosinophilia have been reported.

OVERDOSAGE

In case of overdosage, discontinue medication, treat symptomatically, and institute supportive measures. Dialysis does not alter serum half-life and thus would not be of benefit in treating cases of overdose.

DOSAGE AND ADMINISTRATION

THE DOSAGE OF ORACEA DIFFERS FROM THAT OF DOXYCYCLINE USED TO TREAT INFECTIONS. EXCEEDING THE RECOMMENDED DOSAGE MAY RESULT IN AN INCREASED INCIDENCE OF SIDE EFFECTS INCLUDING THE DEVELOPMENT OF RESISTANT MICROORGANISMS.

One ORACEA Capsule (40 mg) should be taken once daily in the morning on an empty stomach, preferably at least one hour prior to or two hours after meals.

Efficacy beyond 16 weeks and safety beyond 9 months have not been established.

Administration of adequate amounts of fluid along with the capsules is recommended to wash down the capsule to reduce the risk of esophageal irritation and ulceration. (see ADVERSE REACTIONS section).

HOW SUPPLIED

ORACEA (beige opaque capsule printed with CGPI 40) containing doxycycline, USP in an amount equivalent to 40 mg of anhydrous doxycycline. Bottle of 30 (NDC 54868-5676-0).

Storage

All products are to be stored at controlled room temperatures of l5°C-30°C (59°F-86°F) and dispensed in tight, light-resistant containers (USP). Keep out of reach of children.

Patent Information: U.S. Patents 5,789,395; 5,919,775 and patents pending.

Manufactured by:
CardinalHealth
Winchester, KY 40391

Marketed by:
CollaGenex Pharmaceuticals, Inc.
Newtown, PA 18940

May 26, 2006

PRINCIPAL DISPLAY PANEL

ORACEA Capsule, 40 mg